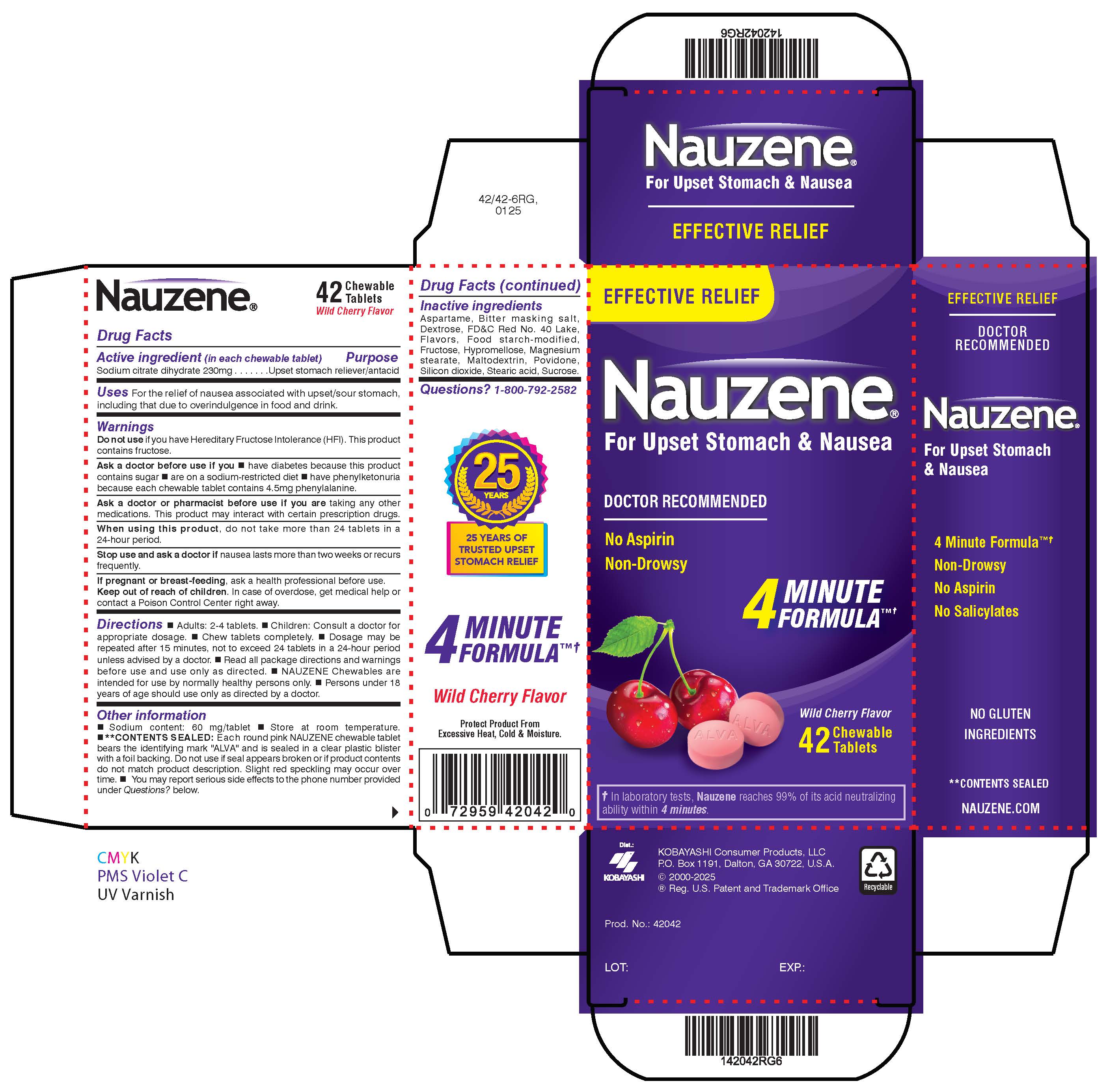 DRUG LABEL: Nauzene
NDC: 52389-242 | Form: TABLET, CHEWABLE
Manufacturer: Kobayashi Healthcare International, Inc.
Category: otc | Type: HUMAN OTC DRUG LABEL
Date: 20250429

ACTIVE INGREDIENTS: TRISODIUM CITRATE DIHYDRATE 230 mg/1 1
INACTIVE INGREDIENTS: ASPARTAME; FD&C RED NO. 40; MAGNESIUM STEARATE; MALTODEXTRIN; SILICON DIOXIDE; STEARIC ACID; DEXTROSE; FRUCTOSE; MODIFIED CORN STARCH (1-OCTENYL SUCCINIC ANHYDRIDE); HYPROMELLOSES; POVIDONE K30; SUCROSE; CHERRY

Nauzene Chewables

Active ingredient (in each chewable tablet)

Sodium citrate dihydrate 230 mg

Purpose

Upset stomach reliever/antacid

Uses

For the relief of nausea associated with upset/sour stomach, including that due to overindulgence in food and drink.

Do not use if you have Hereditary Fructose Intolerance (HFI). This product contains fructose.

Ask a doctor before use if you

- have diabetes because this product contains sugar
- are on a sodium-restricted diet
- have phenylketonuria because each chewable tablet contains 4.5 mg phenylalanine.

Ask a doctor or pharmacist before use if you are taking any other medications. This product may interact with certain prescription drugs.

When using this product, do not take more than 24 tablets in a 24-hour period.

Stop use and ask a doctor if nausea lasts more than two weeks or recurs frequently.

PREGNANCY OR BREAST FEEDING

If pregnant or breastfeeding, ask a health professional before use.

Keep out of reach of children. In case of overdose, get medical help or contact a Poison Control Center right away.

Directions

- Adults: 2 - 4 tablets.
- Children: Consult a doctor for appropriate dosage.
- Chew tablets completely.
- Dosage may be repeated after 15 minutes, not to exceed 24 tablets in a 24-hour period unless advised by a doctor.
- Read all package directions and warning before use and use only as directed.
- Nauzene Chewables are intended for use by normally healthy persons only.
- Persons under 18 years of age should use only as directed by a doctor.

Other information

- Sodium content: 60 mg/tablet
- Store at room temperature.
- **Contents sealed: Each round pink Nauzene chewable tablet bears the identifying mark "ALVA" and is sealed in a clear plastic blister with a foil backing. Do not use if seal appears broken or if product contents do not match product description. Slight red speckling may occur over time.
- Note: Nauzene is not intended as a substitute for a balanced nutritional diet or as an electrolyte replenishment.
- You may report serious side effects to the phone number provided under Questions? below.

Inactive ingredients

Aspartame, bitter masking salt, dextrose, FDC Red No. 40 Lake, flavors, food starch-modified, fructose, hypromellose, magnesium stearate, maltodextrin, povidone, silicon dioxide, stearic acid, sucrose.

Questions? 1-800-792-2582